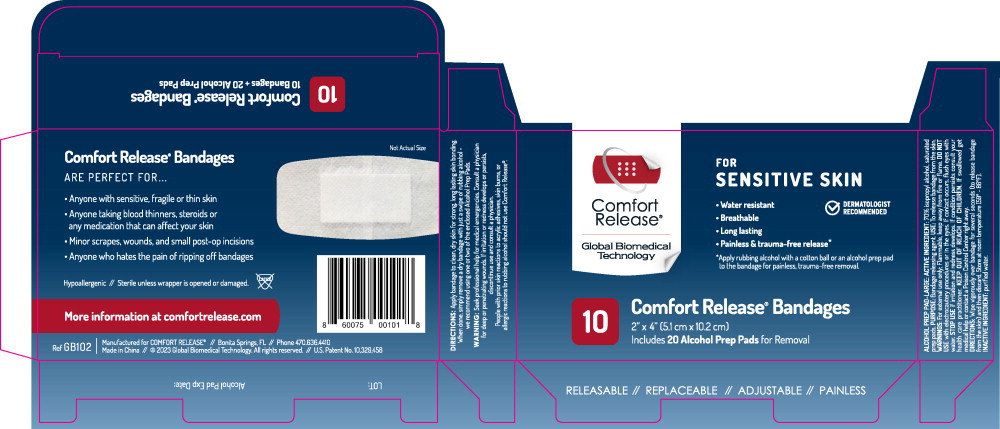 DRUG LABEL: Alcohol Prep Pad-Large

NDC: 72727-0001 | Form: SWAB
Manufacturer: Global Biomedical Technologies, LLC

Category: otc | Type: HUMAN OTC DRUG LABEL
Date: 20250110

ACTIVE INGREDIENTS: ISOPROPYL ALCOHOL
 0.7 mL/1 mL
INACTIVE INGREDIENTS: WATER

ALCOHOL PREP PAD-LARGE:
Drug Facts

ACTIVE INGREDIENT:

70% isopropyl alcohol, saturated prep pads.

PURPOSE:

Bandage releasing agent.

USE:

To release bandage from the skin.

WARNINGS:

For external use only: Flammable, keep away from Fire or flame.

DO NOT USE with electrocautery procedures or in the eyes. If contact occurs, flush eyes with water.

STOP USE if irritation and redness develops. If condition persists consult your health care practitioner.

KEEP OUT OF REACH OF CHILDREN. If swallowed get medical help or contact a Poison Control Center right away.

DIRECTIONS:

Wipe vigorously over bandage for several seconds (to release bandage from the skin) and then discard. Store at room temperature (59° - 86°F).

INACTIVE INGREDIENT:

purified water.

Principal Display Panel – Carton Label

Comfort
Release®

Global Biomedical
Technology

FOR
SENSITIVE SKIN

- Water resistant
- Breathable
- Long lasting
- Painless & trauma-free release*

DERMATOLOGIST
RECOMMENDED

*Apply rubbing alcohol with a cotton ball or an alcohol prep pad
to the bandage for painless, trauma-free removal.

10 Comfort Release® Bandages

2” x 4" [5.1 cm x 10.2 cm]

Includes 20 Alcohol Prep Pads for Removal